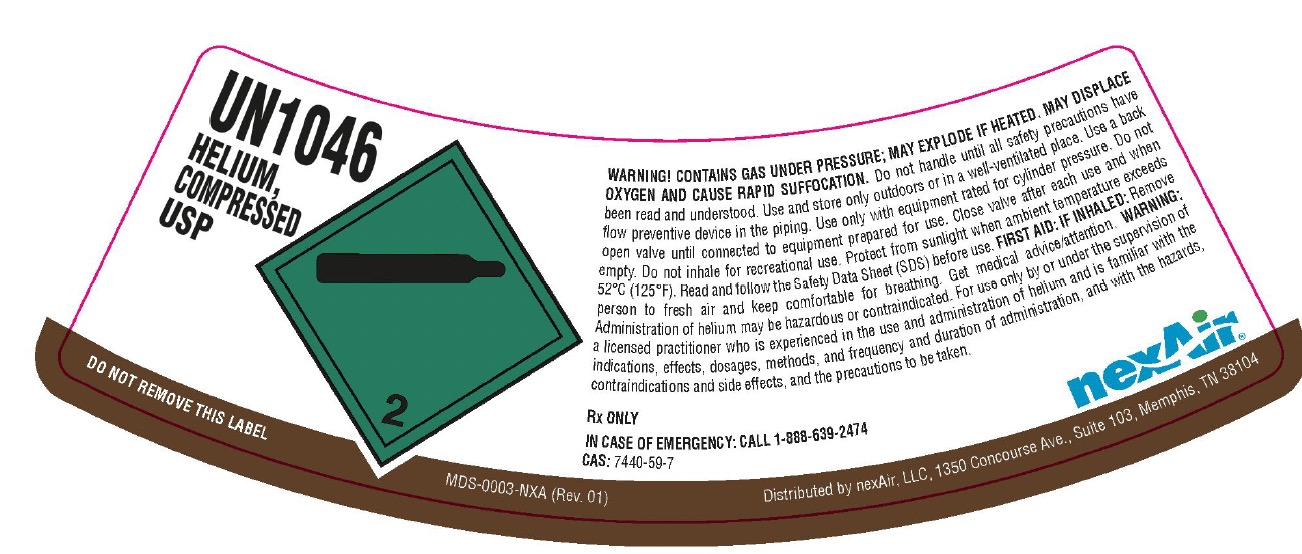 DRUG LABEL: Helium
NDC: 12213-710 | Form: GAS
Manufacturer: NexAir, LLC
Category: prescription | Type: HUMAN PRESCRIPTION DRUG LABEL
Date: 20260113

ACTIVE INGREDIENTS: HELIUM 999 mL/1 L

Helium Label

PACKAGE LABEL

UN1046
HELIUM, COMPRESSED USP
DO NOT REMOVE THIS LABEL
WARNING! CONTAINS GAS UNDER PRESSURE; MAY EXPLODE IF HEATED. MAY DISPLACE OXYGEN AND CAUSE RAPID SUFFOCATION. Do not handle until all safety precautions have been read and understood. Use and store only outdoors or in a well-ventilated place. Use a back flow preventive device in the piping. Use only with equipment rated for cylinder pressure. Do not open valve until connected to equipment prepared for use. Close valve after each use and when empty. Do not inhale for recreational use. Protect form sunlight when ambient temperature exceeds 52 C (125 F). Read and follow the Safety Data Sheet (SDS) before use. FIRST AIR: IF INHALED: Remove person to fresh air and keep comfortable for breathing. Get medical advice/attention. WARNING: Administration of helium may be hazardous or contraindicated. For use only by or under the supervision of a licensed practitioner who is experienced in the use and administration of helium and is familiar with the indications, effects, dosages, methods, and frequency and duration of administration, and with the hazards, contraindications and side effects, and the precautions to be taken.
Rx ONLY
IN CASE OF EMERGENCY: CALL 1-888-639-2474
CAS: 7440-59-7
nexAir
Distributed by nexAir, LLC, 1350 Concourse Ave., Suite 103, Memphis, TN 38104